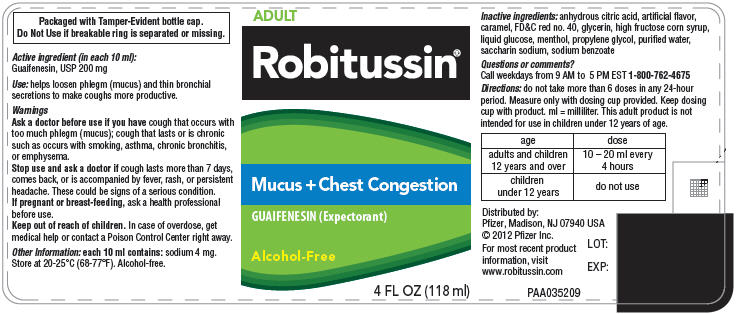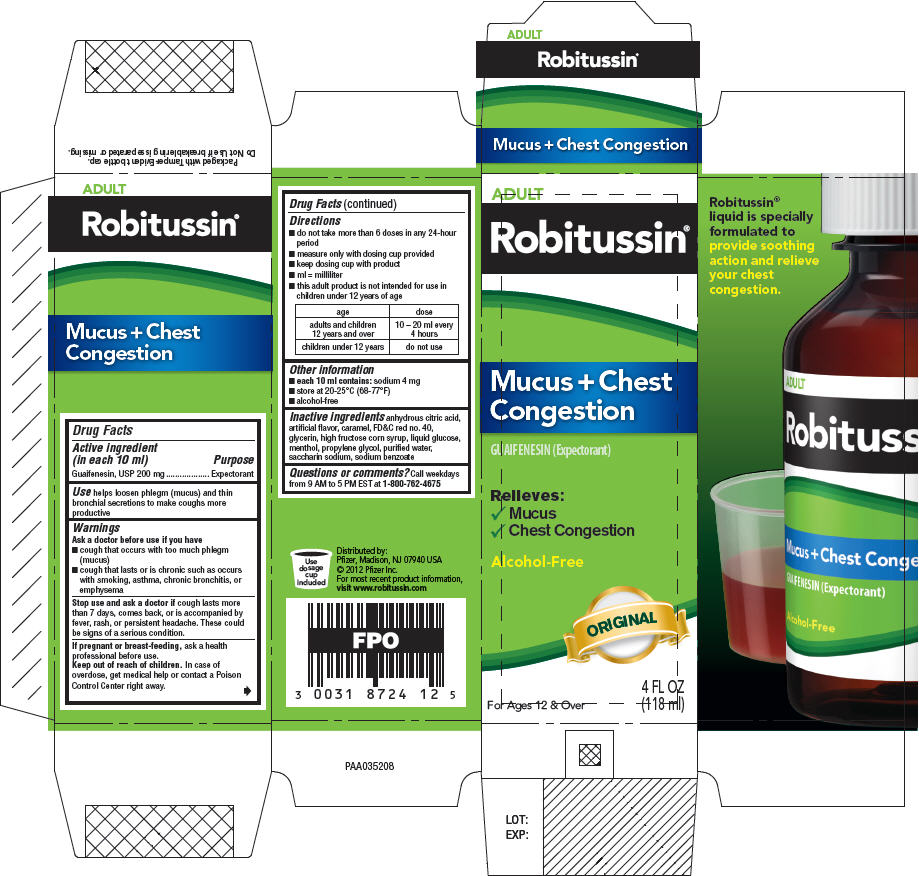 DRUG LABEL: Robitussin Mucus Plus Chest Congestion
NDC: 0031-8724 | Form: LIQUID
Manufacturer: Richmond Division of Wyeth
Category: otc | Type: HUMAN OTC DRUG LABEL
Date: 20150327

ACTIVE INGREDIENTS: GUAIFENESIN 200 mg/10 mL
INACTIVE INGREDIENTS: ANHYDROUS CITRIC ACID; CARAMEL; DEXTROSE; FD&C RED NO. 40; HIGH FRUCTOSE CORN SYRUP; MENTHOL, UNSPECIFIED FORM; PROPYLENE GLYCOL, (R)-; SACCHARIN SODIUM; SODIUM BENZOATE; WATER; GLYCERIN

ROBITUSSIN® MUCUS PLUS CHEST CONGESTION

Drug Facts

Active ingredient (in each 10 mL)

Guaifenesin, USP 200 mg

Purpose

Expectorant

Use

helps loosen phlegm (mucus) and thin bronchial secretions to make coughs more productive

Warnings

Ask a doctor before use if you have

- cough that occurs with too much phlegm (mucus)
- cough that lasts or is chronic such as occurs with smoking, asthma, chronic bronchitis, or emphysema

Stop use and ask a doctor if cough lasts more than 7 days, comes back, or is accompanied by fever, rash, or persistent headache. These could be signs of a serious condition.

PREGNANCY OR BREAST FEEDING

If pregnant or breast-feeding, ask a health professional before use.

Keep out of reach of children. In case of overdose, get medical help or contact a Poison Control Center right away.

Directions

- do not take more than 6 doses in any 24-hour period
- measure only with dosing cup provided
- keep dosing cup with product
- ml=milliliter
- this adult product is not intended for use in children under 12 years of age

age | dose
adults and children 12 years and over | 10-20 ml every 4 hours
children under 12 years | do not use

Other information

- each 10 ml contains: sodium 4 mg
- store at 20-25°C (68-77°F). Do not refrigerate
- alcohol-free

Inactive ingredients

anhydrous citric acid, artificial flavor, caramel, FD&C red no. 40, glycerin, high fructose corn syrup, liquid glucose, menthol, propylene glycol, purified water, saccharin sodium, sodium benzoate

Questions or comments?

Call weekdays from 9 AM to 5 PM EST at 1-800-762-4675

Distributed by:
Pfizer, Madison, NJ 07940 USA

For most recent product information, visit www.robitussin.com

PRINCIPAL DISPLAY PANEL - 118 mL Bottle Label

ADULT

Robitussin®

Mucus + Chest Congestion

GUAIFENESIN (Expectorant)

Alcohol-Free

4 FL OZ (118 ml)

PRINCIPAL DISPLAY PANEL - 118 mL Bottle Carton

ADULT

Robitussin®

Mucus + Chest
Congestion

GUAIFENESIN (Expectorant)

Relieves:

✓ Mucus
✓ Chest Congestion

Alcohol-Free

ORIGINAL

For Ages 12 & Over

4 FL OZ
(118 ml)